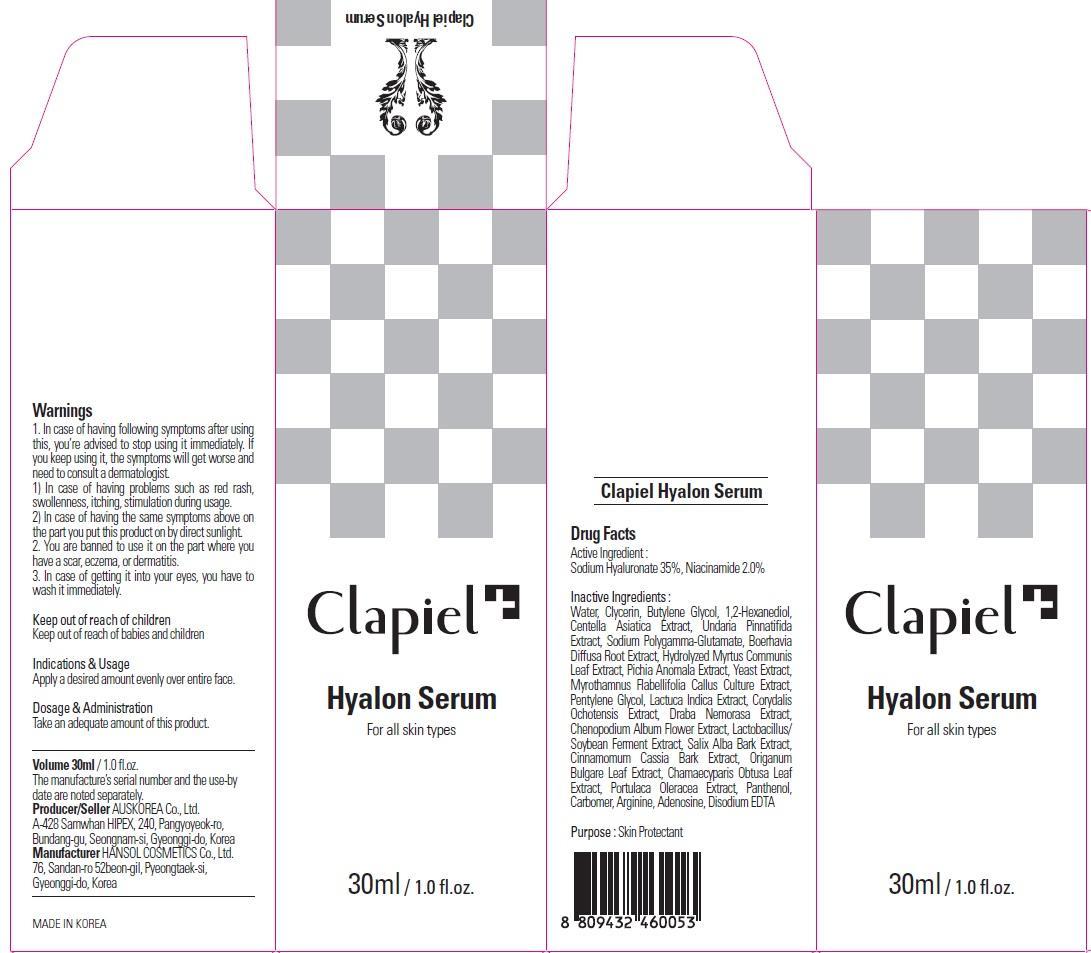 DRUG LABEL: Clapiel Hyalon Serum
NDC: 69977-020 | Form: CREAM
Manufacturer: AUS KOREA CO., LTD.
Category: otc | Type: HUMAN OTC DRUG LABEL
Date: 20150724

ACTIVE INGREDIENTS: NIACINAMIDE 0.6 mg/30 mL; HYALURONATE SODIUM 10.5 mg/30 mL
INACTIVE INGREDIENTS: Water; Glycerin

ACTIVE INGREDIENT

Active Ingredient: Sodium Hyaluronate 35%, Niacinamide 2.0%

INACTIVE INGREDIENT

Inactive Ingredients: Water, Glycerin, Butylene Glycol, 1,2-Hexanediol, Centella Asiatica Extract, Undaria Pinnatifida Extract, Sodium Polygamma-Glutamate, Boerhavia Diffusa Root Extract, Hydrolyzed Myrtus Communis Leaf Extract, Pichia Anomala Extract, Yeast Extract, Myrothamnus Flabellifolia Callus Culture Extract, Pentylene Glycol, Lactuca Indica Extract, Corydalis Ochotensis Extract, Draba Nemorasa Extract, Chenopodium Album Flower Extract, Lactobacillus/Soybean Ferment Extract, Salix Alba Bark Extract, Cinnamomum Cassia Bark Extract, Origanum Bulgare Leaf Extract, Chamaecyparis Obtusa Leaf Extract, Portulaca Oleracea Extract, Panthenol, Carbomer, Arginine, Adenosine, Disodium EDTA

PURPOSE

Purpose: Skin Protectant

WARNINGS

Warnings: 1. In case of having following symptoms after using this, you’re advised to stop using it immediately. If you keep using it, the symptoms will get worse and need to consult a dermatologist. 1) In case of having problems such as red rash, swollenness, itching, stimulation during usage. 2) In case of having the same symptoms above on the part you put this product on by direct sunlight. 2. You are banned to use it on the part where you have a scar, eczema, or dermatitis. 3. In case of getting it into your eyes, you have to wash it immediately.

KEEP OUT OF REACH OF CHILDREN

Keep out of reach of babies and children

INDICATIONS & USAGE

Indications & Usage: Apply a desired amount evenly over entire face.

DOSAGE & ADMINISTRATION

Dosage & Administration: Take an adequate amount of this product